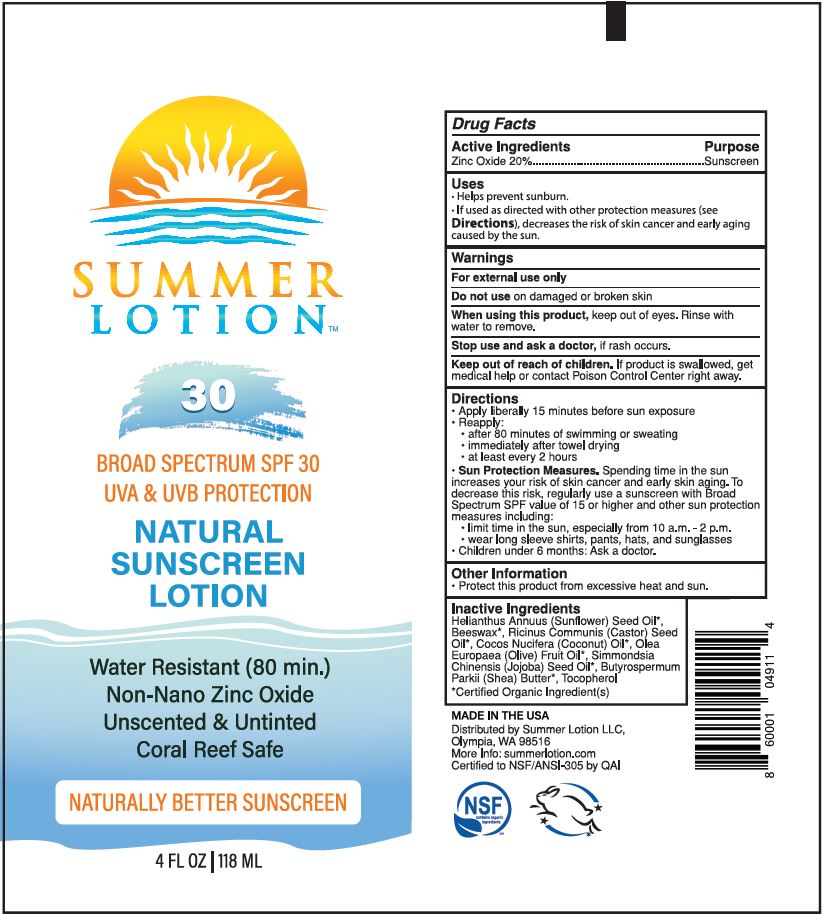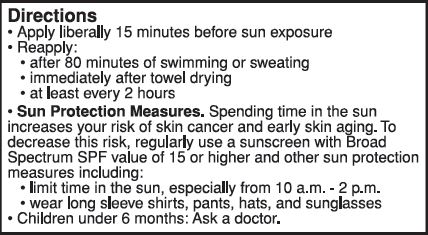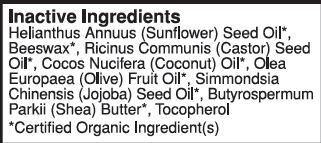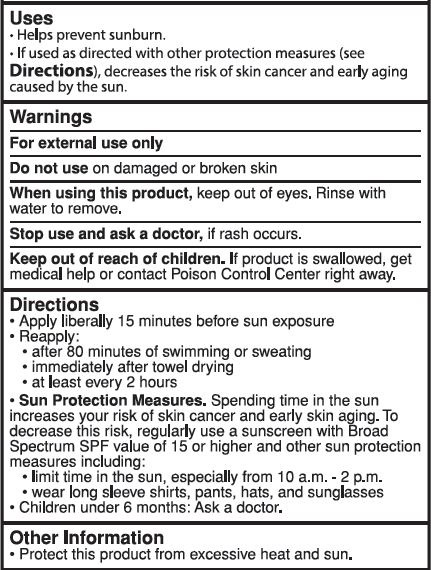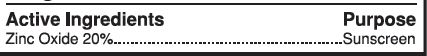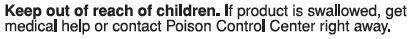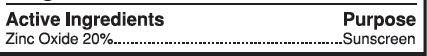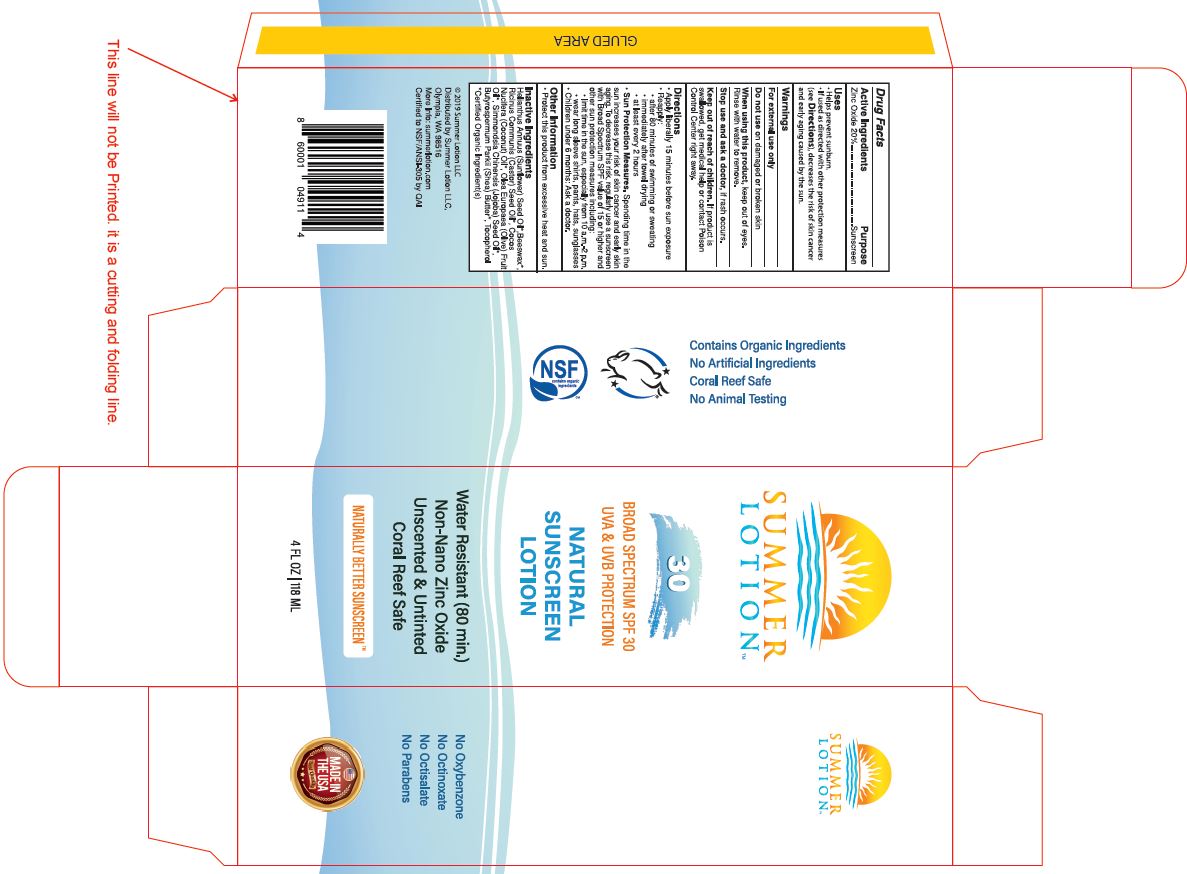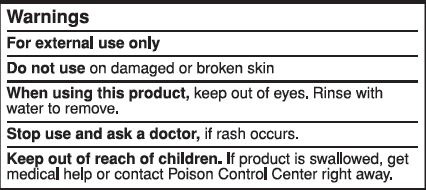 DRUG LABEL: SUNSCREEN
NDC: 62932-205 | Form: OINTMENT
Manufacturer: Private Label Select Ltd CO
Category: otc | Type: HUMAN OTC DRUG LABEL
Date: 20191228

ACTIVE INGREDIENTS: ZINC OXIDE 20 g/100 g
INACTIVE INGREDIENTS: CASTOR OIL; JOJOBA OIL; TOCOPHEROL; COCONUT OIL; OLIVE OIL; SHEA BUTTER; WHITE WAX; SUNFLOWER OIL

Summer Lotion SPF 30 Natural Sunscreen Lotion